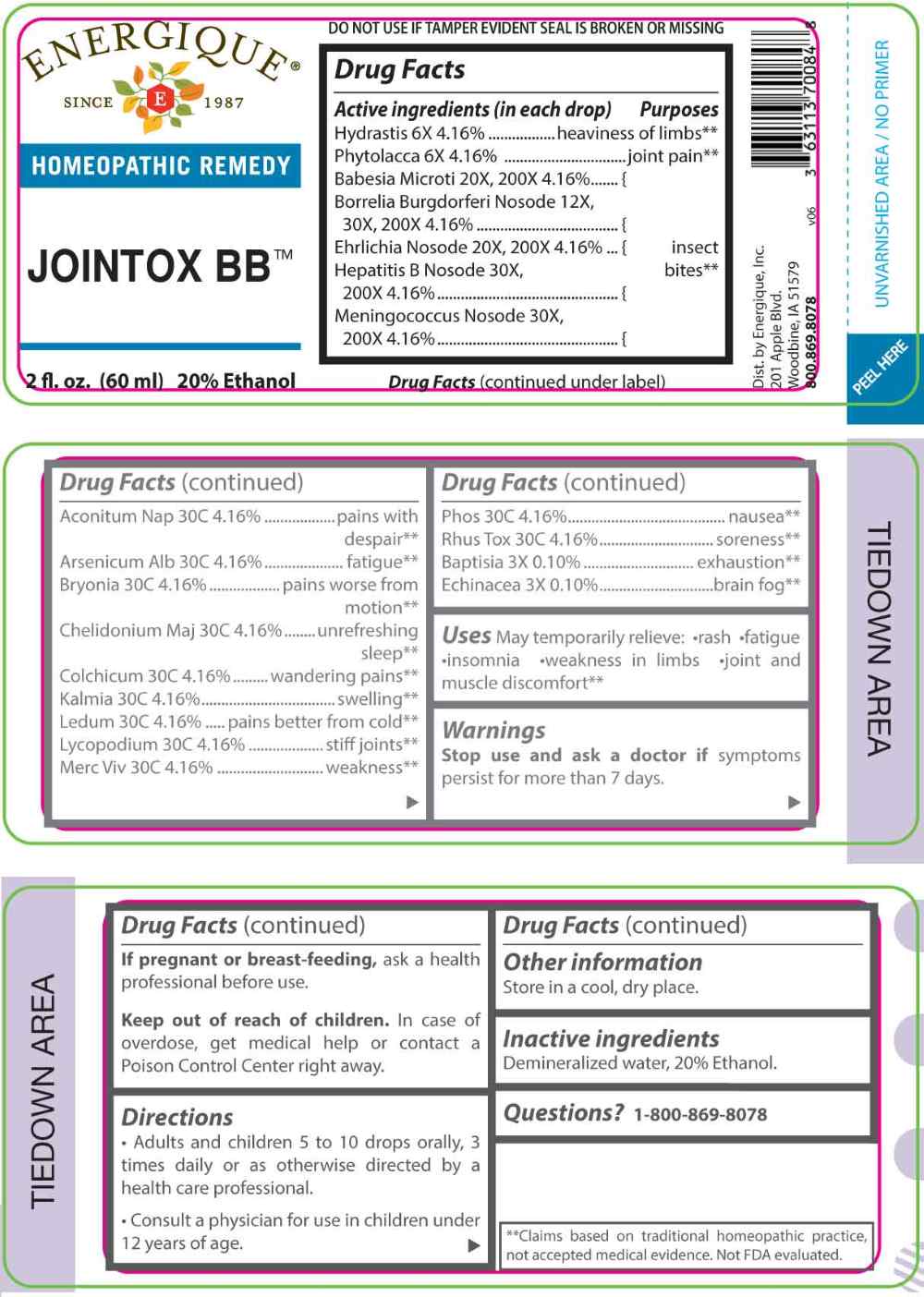 DRUG LABEL: Jointox BB
NDC: 44911-0743 | Form: LIQUID
Manufacturer: Energique, Inc.
Category: homeopathic | Type: HUMAN OTC DRUG LABEL
Date: 20260105

ACTIVE INGREDIENTS: BAPTISIA TINCTORIA ROOT 3 [hp_X]/1 mL; ECHINACEA ANGUSTIFOLIA WHOLE 3 [hp_X]/1 mL; GOLDENSEAL 6 [hp_X]/1 mL; PHYTOLACCA AMERICANA ROOT 6 [hp_X]/1 mL; BORRELIA BURGDORFERI 12 [hp_X]/1 mL; BABESIA MICROTI 20 [hp_X]/1 mL; EHRLICHIA CANIS 20 [hp_X]/1 mL; HEPATITIS B VIRUS 30 [hp_X]/1 mL; NEISSERIA MENINGITIDIS 30 [hp_X]/1 mL; ACONITUM NAPELLUS WHOLE 30 [hp_C]/1 mL; ARSENIC TRIOXIDE 30 [hp_C]/1 mL; BRYONIA ALBA ROOT 30 [hp_C]/1 mL; CHELIDONIUM MAJUS WHOLE 30 [hp_C]/1 mL; COLCHICUM AUTUMNALE BULB 30 [hp_C]/1 mL; KALMIA LATIFOLIA LEAF 30 [hp_C]/1 mL; RHODODENDRON TOMENTOSUM LEAFY TWIG 30 [hp_C]/1 mL; LYCOPODIUM CLAVATUM SPORE 30 [hp_C]/1 mL; MERCURY 30 [hp_C]/1 mL; PHOSPHORUS 30 [hp_C]/1 mL; TOXICODENDRON PUBESCENS LEAF 30 [hp_C]/1 mL
INACTIVE INGREDIENTS: WATER; ALCOHOL

DRUG FACTS:

ACTIVE INGREDIENTS:

(in each drop) Hydrastis Canadensis 6X 4.16%, Phytolacca Decandra 6X 4.16%, Babesia Microti 20X, 200X 4.16%, Borrelia Burgdorferi Nosode 12X, 30X, 200X4.16%, Ehrlichia Nosode 20X, 200X 4.16%, Hepatitis B Nosode 30X, 200X 4.16%, Meningococcus Nosode 30X, 200X 4.16%, Aconitum Napellus 30C 4.16%, Arsenicum Album 30C 4.16%, Bryonia 30C 4.16%, Chelidonium Majus 30C 4.16%, Colchicum Autumnale 30C 4.16%, Kalmia Latifolia 30C 4.16%, Ledum Palustre 30C 4.16%, Lycopodium Clavatum 30C 4.16%, Mercurius Vivus 30C 4.16%, Phosphorus 30C 4.16%, Rhus Tox 30C 4.16%, Baptisia Tinctoria 3X 0.10%, Echinacea 3X 0.10%.

PURPOSE:

Hydrastis Canadensis – heaviness of limbs,** Phytolacca Decandra – joint pain,** Babesia Microti – insect bites,** Borrelia Burgdorferi Nosode – insect bites,** Ehrlichia Nosode – insect bites,** Hepatitis B Nosode – insect bites,** Meningococcus Nosode – insect bites,** Aconitum Napellus – pains with despair,** Arsenicum Album - fatigue,** Bryonia – pains worse from motion,** Chelidonium Majus – unrefreshing sleep,** Colchicum Autumnale – wandering pains,** Kalmia Latifolia - swelling,** Ledum Palustre – pains better from cold,** Lycopodium Clavatum – stiff joints,** Mercurius Vivus - weakness,** Phosphorus - nausea,** Rhus Tox - soreness,** Baptisia Tinctoria - exhaustion,** Echinacea – brain fog**

**Claims based on traditional homeopathic practice, not accepted medical evidence. Not FDA evaluated.

USES:

May temporarily relieve: •rash •fatigue •insomnia •weakness in limbs •joint and muscle discomfort**

**Claims based on traditional homeopathic practice, not accepted medical evidence. Not FDA evaluated.

WARNINGS:

Stop use and ask a doctor if symptoms persist for more than 7 days.

If pregnant or breast-feeding, ask a health professional before use.

Keep out of reach of children. In case of overdose, get medical help or contact a Poison Control Center right away.

DO NOT USE IF TAMPER EVIDENT SEAL IS BROKEN OR MISSING

Store in a cool, dry place.

KEEP OUT OF REACH OF CHILDREN:

In case of overdose, get medical help or contact a Poison Control Center right away.

DIRECTIONS:

• Adults and children 5 to 10 drops orally, 3 times daily or as otherwise directed by a health care professional.

Consult a physician for use in children under 12 years of age.

INACTIVE INGREDIENTS:

Demineralized water, 20% Ethanol.

QUESTIONS:

Dist. by Energique, Inc.

201 Apple Blvd.

Woodbine, IA 51579

800.869.8078

PACKAGE LABEL DISPLAY:

ENERGIQUE

SINCE 1987

HOMEOPATHIC REMEDY

JOINTOX BB

2 fl. oz. (60 ml)